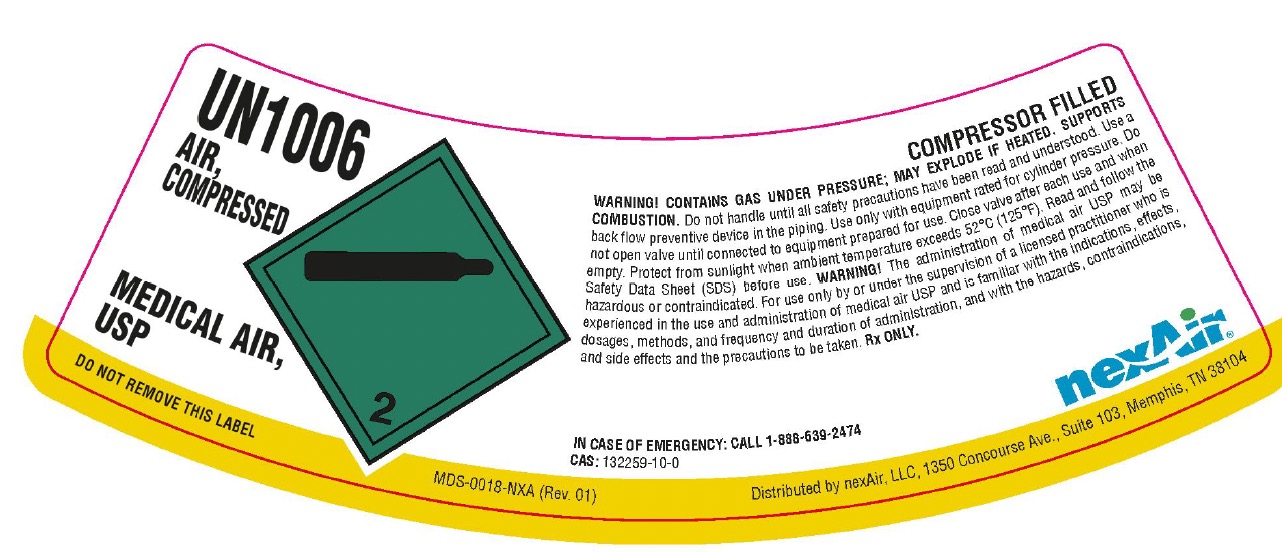 DRUG LABEL: Air
NDC: 12213-700 | Form: GAS
Manufacturer: NexAir, LLC
Category: prescription | Type: HUMAN PRESCRIPTION DRUG LABEL
Date: 20251031

ACTIVE INGREDIENTS: AIR 1000 mL/1 L

Air

PACKAGE LABEL

UN1006

AIR, COMPRESSED

MEDICAL AIR, USP

DO NOT REMOVE THIS LABEL

COMPRESSOR FILLED

WARNING! CONTAINS GAS UNDER PRESSURE; MAY EXPLODE IF HEATED. SUPPORTS COMBUSTION. Do not handle until all safety precautions have been read and understood. Use a back flow preventive device in the piping. Use only with equipment rated for cylinder pressure. Do not open valve until connected to equipment prepared for use. Close valve after each use and when empty. Protect from sunlight when ambient temperature exceeds 52 C (125 F). Read and follow the Safety Data Sheet (SDS) before use. WARNING! The administration of medical air USP may be hazardous or contraindicated. For use only by or under the supervision of a licensed practitioner who is experienced in the use and administration of medical air USP and is familiar with the indications, effects, dosages, methods, and frequency and duration of administration, and with the hazards, contraindications, and side effects and the precautions to be taken. Rx ONLY.

IN CASE OF EMERGENCY: CALL 1-888-639-2474

CAS: 132259-10-0

nexAir

Distributed by nexAir, LLC, 1350 Concourse Ave., Suite 103, Memphis, TN 38104